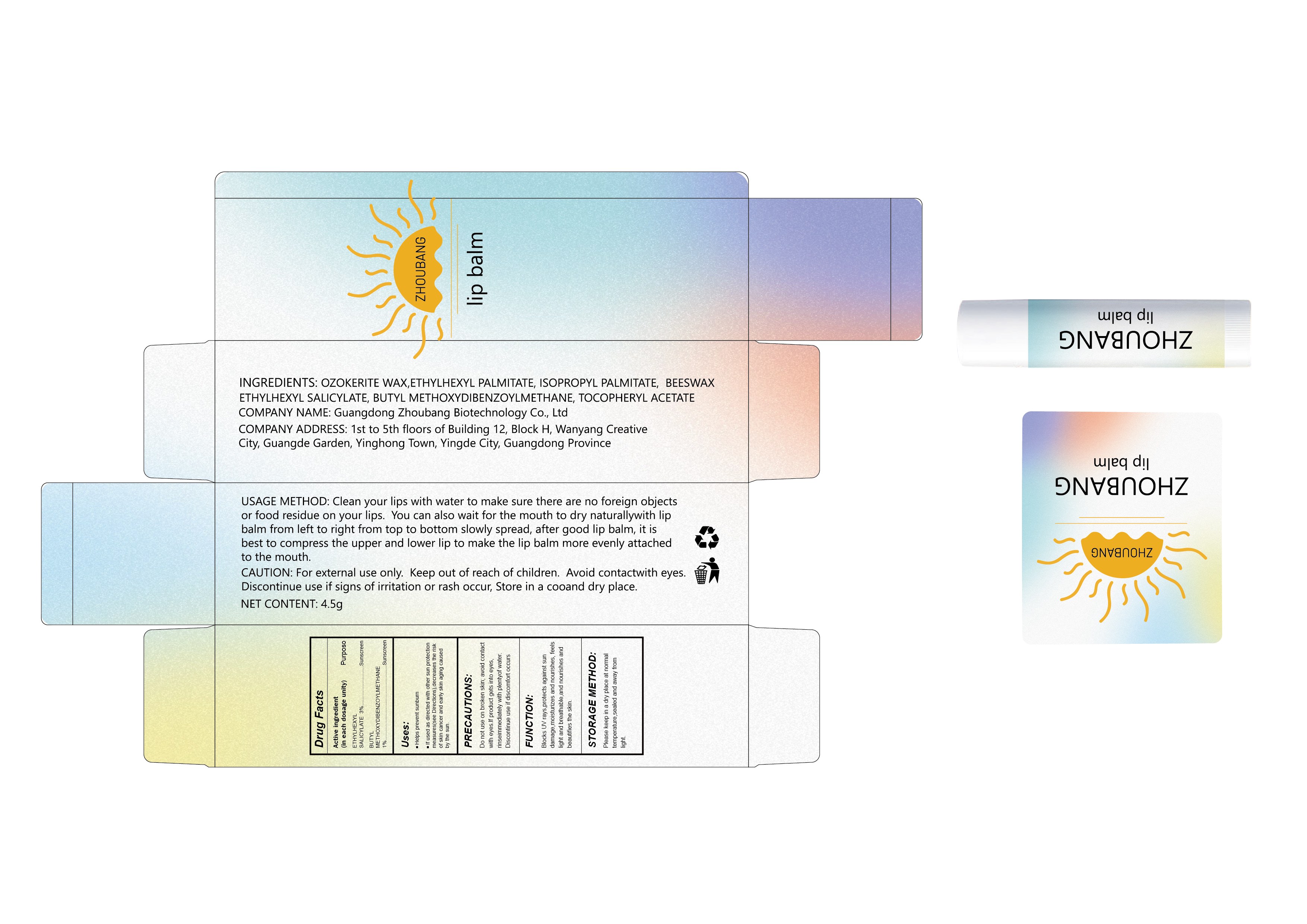 DRUG LABEL: Sunscreen lip balm
NDC: 87357-002 | Form: LIPSTICK
Manufacturer: Guangdong Zhoubang Biotechnology Co., Ltd
Category: otc | Type: HUMAN OTC DRUG LABEL
Date: 20260121

ACTIVE INGREDIENTS: BUTYL METHOXYDIBENZOYLMETHANE 1 g/100 g; ETHYLHEXYL SALICYLATE 3 g/100 g
INACTIVE INGREDIENTS: CERESIN; ISOPROPYL PALMITATE; ETHYLHEXYL PALMITATE; BEESWAX; .ALPHA.-TOCOPHEROL ACETATE; DIISOSTEARYL MALATE

INACTIVE INGREDIENT

CERESIN
ETHYLHEXYL PALMITATE
ISOPROPYL PALMITATE
BEESWAX
DIISOSTEARYL MALATE

.ALPHA.-TOCOPHEROL ACETATE

DOSAGE AND ADMINISTRATION

Clean your lips with water to make sure there are no foreign objects or food residue on your lips. You can also wait for the mouth to dry naturallywith lip balm from left to right from top to bottom slowly spread, after good lip balm, it is best to compress the upper and lower lip to make the lip balm more evenly attached to the mouth.

WARNINGS

For external use only. Keep out of reach of children. Avoid contactwith eyes.Discontinue use if signs of irritation or rash occur, Store in a cooand dry place.

ACTIVE INGREDIENT

ETHYLHEXYL SALICYLATE 3%
BUTYL METHOXYDIBENZOYLMETHANE 1%

Keep out of reach of children.Do not use on broken skin; avoid contact with eyes.lf product gets into eyes, rinseimmediately with plentyof water.Discontinue use if discomfort occurs

PURPOSE

Sun protection

INDICATIONS AND USAGE

Helps prevent sunburn
If used as directed with other sun protection measures(see Directions),decreases the risk of skin cancer and early skin aging caused
by the sun.